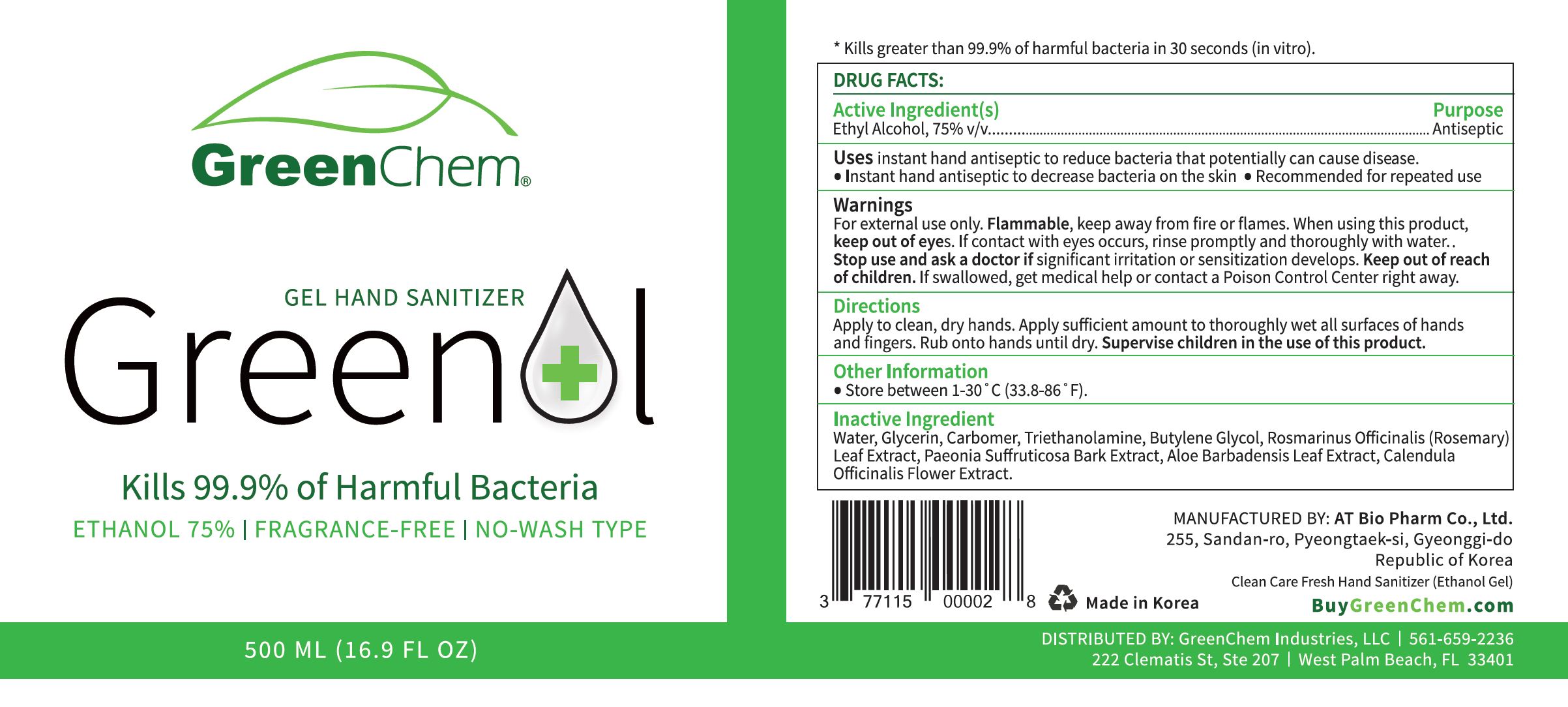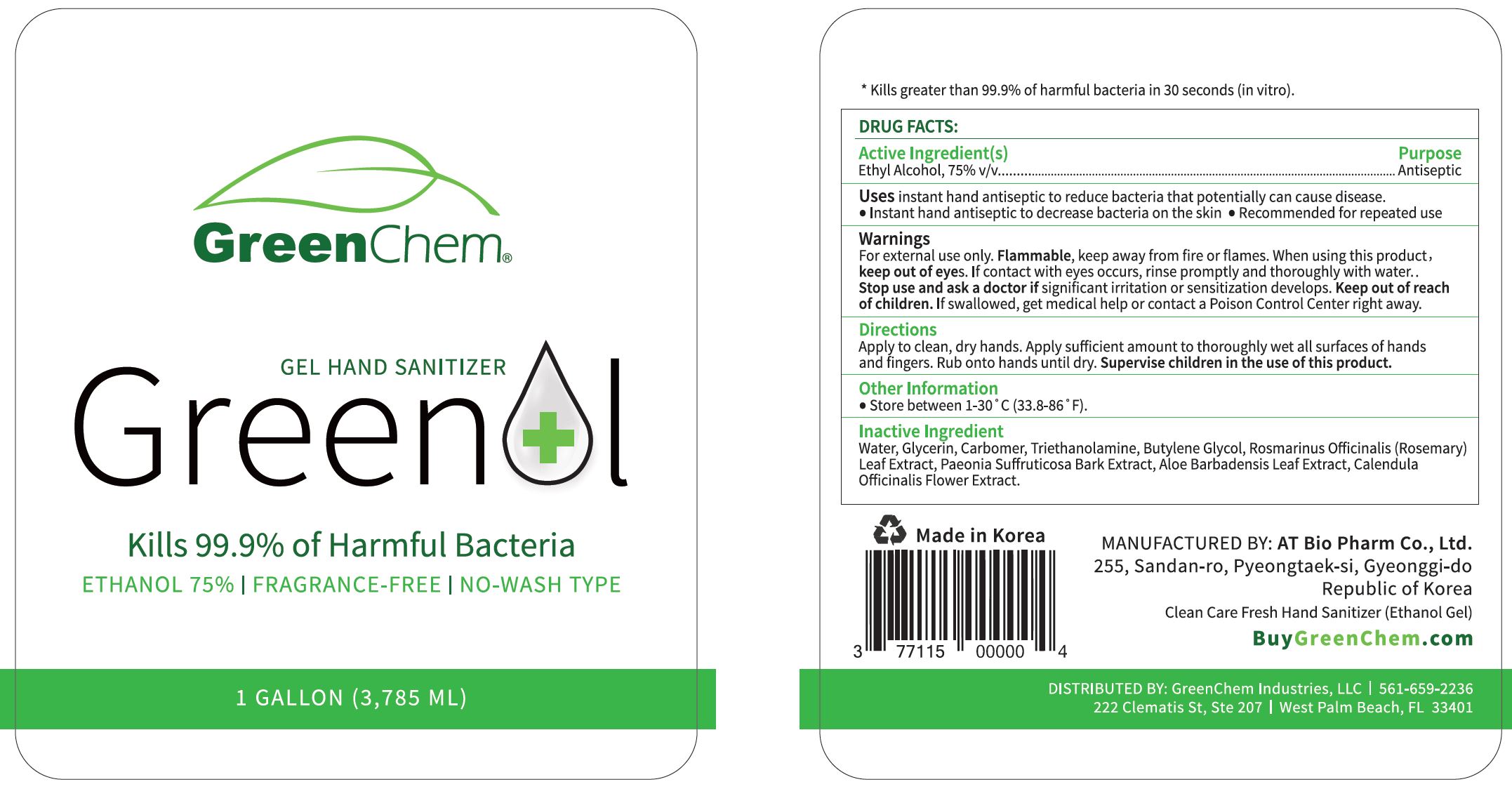 DRUG LABEL: Clean Care Fresh Hand Sanitizer (Ethanol gel)
NDC: 73932-0017 | Form: GEL
Manufacturer: AT Bio Pharm Co Ltd
Category: otc | Type: HUMAN OTC DRUG LABEL
Date: 20210225

ACTIVE INGREDIENTS: ALCOHOL 75 mL/100 mL
INACTIVE INGREDIENTS: ROSEMARY OIL; PAEONIA SUFFRUTICOSA ROOT BARK; CALENDULA OFFICINALIS FLOWER; ALOE VERA LEAF; GLYCERIN; TROLAMINE; WATER; BUTYLENE GLYCOL

Drug Facts

ACTIVE INGREDIENT

alcohol

INACTIVE INGREDIENT

Water, Glycerin, butylene glycol, carbomer, triethanolamine, rosmarinus officinalis (rosemary) leaf extract, paeonia suffruticosa bark extract, aloe barbadensis leaf extract, calendula officianalis flower extract

PURPOSE

Antiseptic

instant healthcare personnel hand antiseptic to reduce bacteria that potentially can cause disease

instant hand antiseptic to decrease bacteria on the skin
recommended for repeated use

hand sanitizer to help reduce bacteria on the skin

KEEP OUT OF REACH OF THE CHILDREN

INDICATIONS AND USAGE

Apply to clean, dry hands. Apply sufficient amount to thoroughly wet all surfaces of hands and fingers. Rub onto hands until dry.

Supervise children in the use of this product.

Dispense appropriate amount on your palm and thoroughly spread on both hands and rub into the skin until dry

WARNINGS

For external use only.

Flammable, keep away from fire or flame.

When using this product keep out of eyes. If contact with eyes occurs, rinse promptly and thoroughly with water.

Stop use and ask a doctor if significant irritation or sensitization develops.

Keep out of reach of children. If swallowed, get medical help or contact a Poison Control Center right away.

DOSAGE AND ADMINISTRATION

for external use only